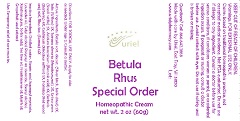 DRUG LABEL: Betula Rhus Special Order
NDC: 48951-2114 | Form: CREAM
Manufacturer: Uriel Pharmacy Inc.
Category: homeopathic | Type: HUMAN OTC DRUG LABEL
Date: 20181114

ACTIVE INGREDIENTS: BETULA PUBESCENS BARK 2 [hp_X]/1 g; SAGE 2 [hp_X]/1 g; FILIPENDULA ULMARIA ROOT 2 [hp_X]/1 g; URTICA URENS 2 [hp_X]/1 g; BENZOIC ACID 3 [hp_X]/1 g; BERBERIS VULGARIS ROOT BARK 4 [hp_X]/1 g; COLCHICUM AUTUMNALE WHOLE 5 [hp_X]/1 g; FORMICA RUFA 10 [hp_X]/1 g; TOXICODENDRON PUBESCENS LEAF 12 [hp_X]/1 g
INACTIVE INGREDIENTS: TEA TREE OIL; WATER; STEARIC ACID; ISOPROPYL MYRISTATE; LAVENDER OIL; CETYL ALCOHOL; POLYOXYL 40 STEARATE; STEARYL ALCOHOL; XANTHAN GUM; SORBIC ACID; FRANKINCENSE OIL; MYRRH OIL; CITRUS PARADISI SEED

Betula Rhus Special Order

INDICATIONS AND USAGE

Directions: FOR TOPICAL USE ONLY.

DOSAGE AND ADMINISTRATION

Apply to skin as needed. Under age 2: Consult a doctor.

ACTIVE INGREDIENT

Active Ingredients: Betula cort. decoct. (Silver birch, bark dried) 2X, Salix (Willow) 2X, Spiraea ulmaria (Meadowsweet) 2X, Urtica urens (Small nettle) 2X, Acidum benzoicum (Benzoic acid) 3X, Berberis (Barberry) 4X, Colchicum (Meadow saffron) 5X, Formica (Red wood ant) 10X, Rhus tox. (Sumac) 12X

Inactive Ingredient: Distilled water, Stearic acid, Isopropyl myristate, Lavender oil, Cetyl alcohol, Polyoxyl 40 stearate, Stearyl alcohol, Xanthan gum, Sorbic acid, Tea tree oil, Frankincense oil, Myrrh oil, Grapefruit seed extract

PURPOSE

Use: Temporary relief of sore muscles.

KEEP OUT OF REACH OF CHILDREN.

Warnings: FOR EXTERNAL USE ONLY.
Claims based on traditional homeopathic practice, not accepted medical evidence. Not FDA evaluated. Do not use if allergic to any ingredient. Consult a doctor before use for serious conditions, if conditions worsen or persist, or accidental ingestion occurs. If pregnant or nursing, consult a doctor before use. Avoid contact with eyes. Do not use if safety seal is broken or missing.

QUESTIONS

Questions? Call 866.642.2858 Made with care by Uriel, East Troy, WI 53120 www.urielpharmacy.com